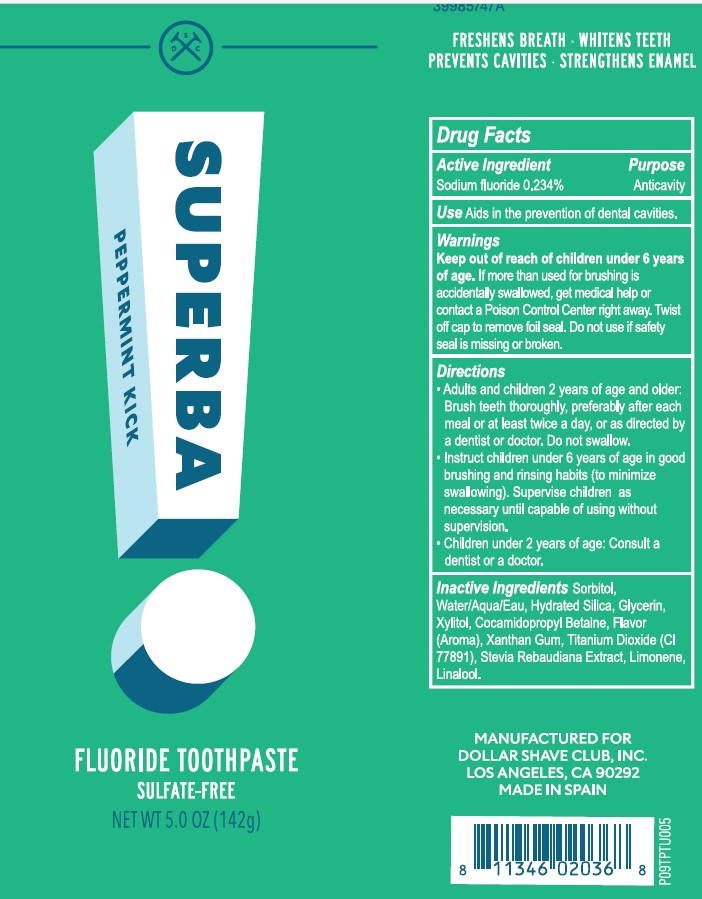 DRUG LABEL: Superba
NDC: 69522-1113 | Form: PASTE
Manufacturer: Dollar Shave Club, Inc.
Category: otc | Type: HUMAN OTC DRUG LABEL
Date: 20211102

ACTIVE INGREDIENTS: SODIUM FLUORIDE 1 mg/1 g
INACTIVE INGREDIENTS: SORBITOL; STEVIA REBAUDIUNA LEAF; XYLITOL; COCAMIDOPROPYL BETAINE; LINALOOL, (+)-; WATER; HYDRATED SILICA; GLYCERIN; XANTHAN GUM; TITANIUM DIOXIDE; LIMONENE, (+)-

Dollar Shave Club Superba toothpaste

Active Ingredient Sodium fluoride 0.234%

Purpose Anticavity

INDICATIONS AND USAGE

Use Aids in the prevention of dental cavities

Warnings

Keep out of reach of children under 6 years of age. If more than used for brushing is accidentally swallowed, get medical help or contact a Poison Control Center right away. Twist off cap to remove foil seal. Do not use if safety seal is missing or boken.

Directions

- Adults and children 2 years of age and older: Brush teeth thoroughly, preferably after each meal or at least twice a day, or as directed by a dentist or doctor. Do not swallow.
- Instruct children under 6 years of age in good brushing and rinsing habits (to minimize swallowing). Supervise chldren as necessary until capable of using without supervision.
- Children under 2 years of age: Consult a dentist or a doctor.

INACTIVE INGREDIENT

Inactive Ingredients Sorbitol, Water/Aqua/Eau, Hydrated Silica, Glycerin, Xylitol, Cocamidopropyl Betain, Flavor (Aroma), Xanthan Gum, Titanium Dioxide (CI 77891), Stevia Rebaudiana Extract, Limonene, Linalool.

PACKAGE LABEL

SUPERBA

PEPPERMINT KICK

FLUORIDE TOOTHPASTE

SULFATE-FREE

NET WT 5.0 OZ (142g)

MANUFACTURED FOR

DOLLAR SHAVE CLUB, INC.

LOS ANGELES, CA 90292

MADE IN SPAIN